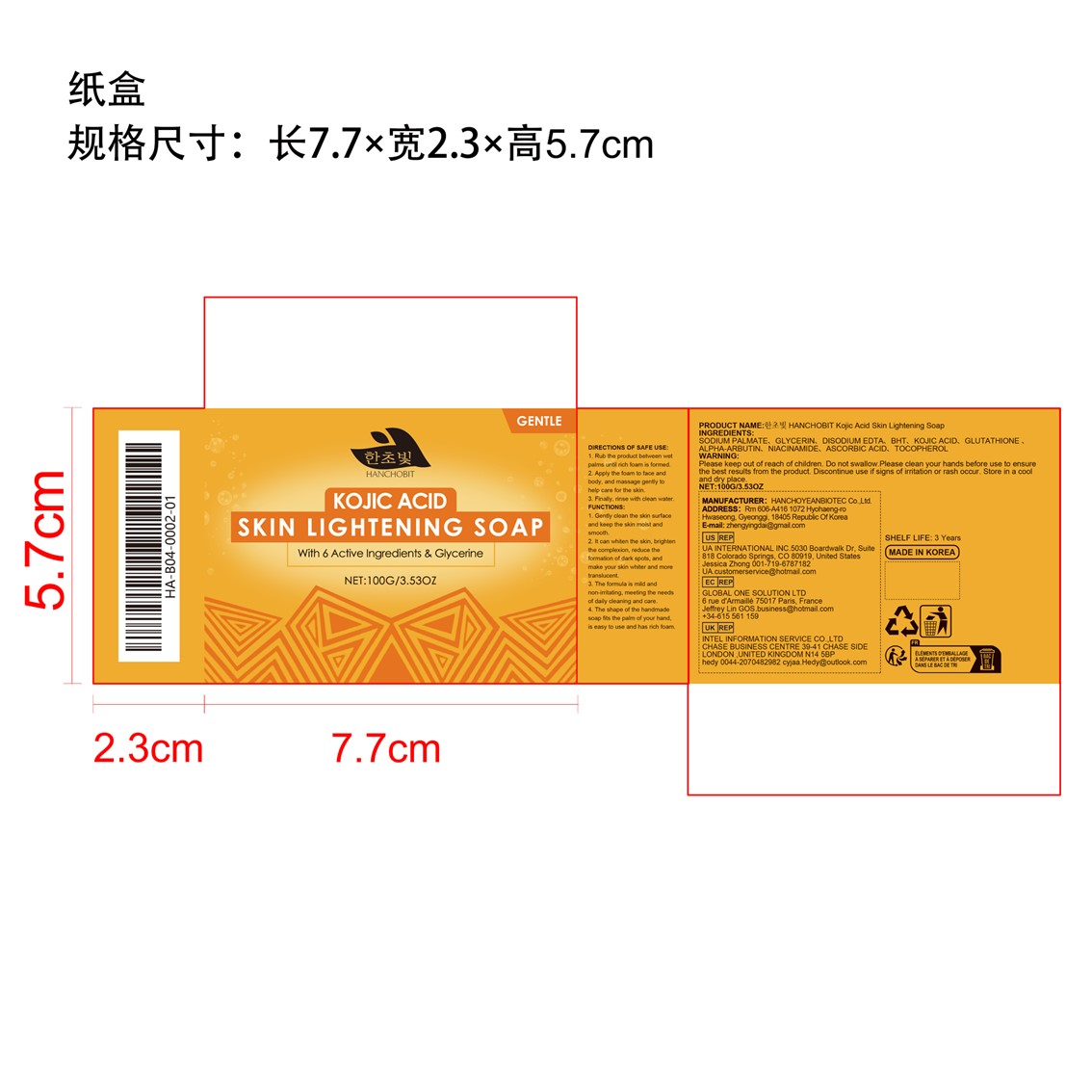 DRUG LABEL: GLUTATHIONE
NDC: 85164-001 | Form: SOAP
Manufacturer: HANCHOYEANBIOTEC Co.,Ltd.
Category: otc | Type: HUMAN OTC DRUG LABEL
Date: 20251127

ACTIVE INGREDIENTS: TOCOPHEROL 0.1 g/100 g; GLUTATHIONE 0.1 g/100 g; ALPHA-ARBUTIN 0.1 g/100 g; ASCORBIC ACID 0.1 g/100 g
INACTIVE INGREDIENTS: BUTYLATED HYDROXYTOLUENE; SODIUM PALMATE; GLYCERIN; KOJIC ACID; EDETATE DISODIUM; NIACINAMIDE

ingredients

SODIUM GLYCERIN、DISODIUM EDTA、BHT、KOJIC ACID、GLUTATHIONE、ALPHA-ARBUTIN、NIACINAMIDE、ASCORBIC ACID、TOCOPHEROL

Functions

1. Gently clean the skin surfaceand keep the skin moist andsmooth.

2. lt can whiten the skin, brightenthe complexion, reduce theformation of dark spots, andmake your skin whiter and moretranslucent.
3. The formula is mild andnon-irritating, meeting the needsof daily cleaning and care.

4. The shape of the handmadesoap fits the palm of your hand,is easy to use and has rich foam.

INDICATIONS AND USAGE

none

Warning

Please keep out of reach of children.

Do not swallow.Please clean your hands before use to ensure the best results from the product.

Discontinue use if signs of irritation or rash occur. Store in a cool and dry place.

DO NOT USE

none

Warning

Please clean your hands before use to ensure the best results from the product.

Warning

Discontinue use if signs of irritation or rash occur. Store in a cool and dry place.

warning

Please keep out of reach of children.

Direction of safe use

1. Rub the product between wetpalms until rich foam is formed.2. Apply the foam to face andbody, and massage gently tohelp care for the skin.3. Finally, rinse with clean water.

warning

Store in a cool
and dry place.

INACTIVE INGREDIENT

NONE